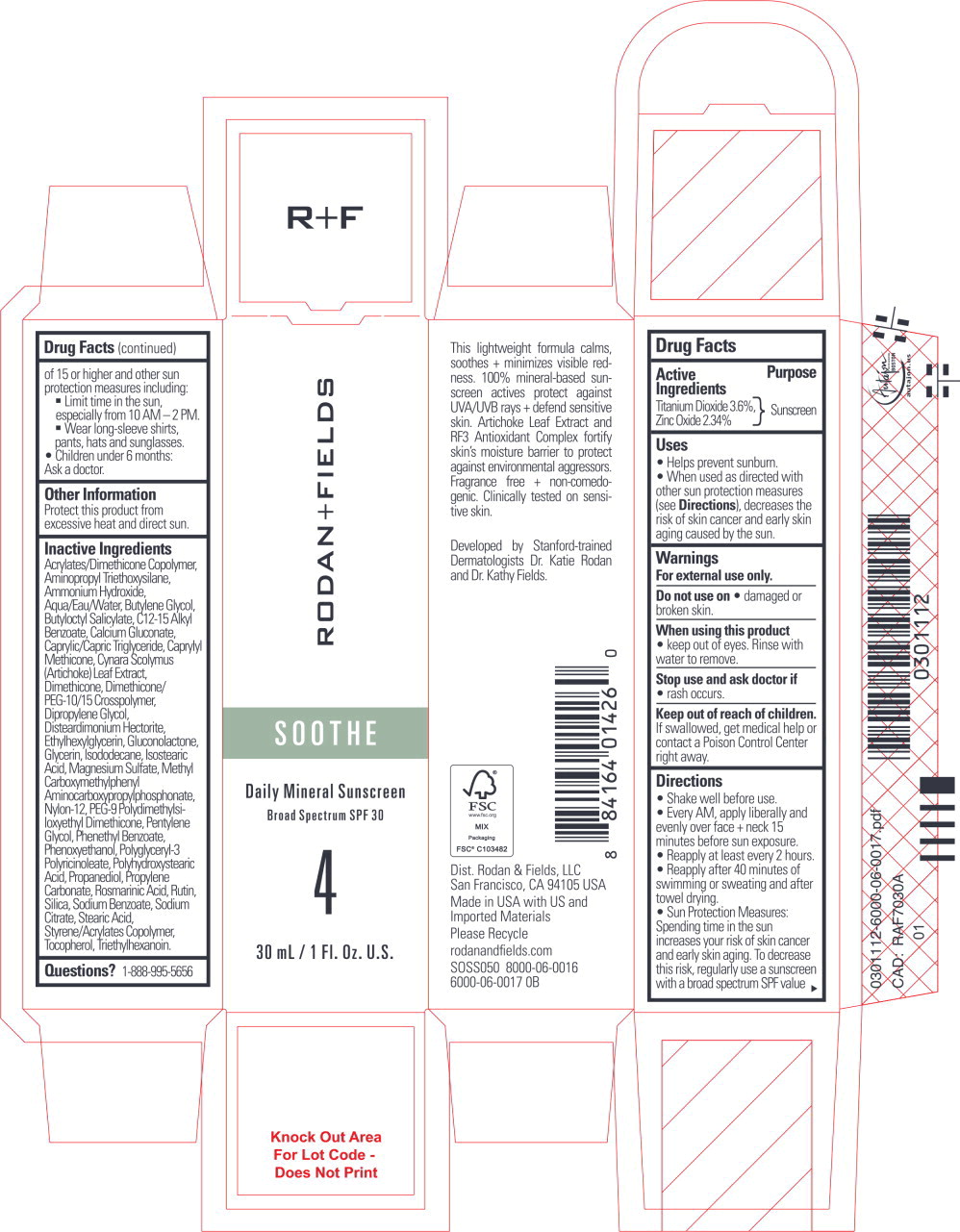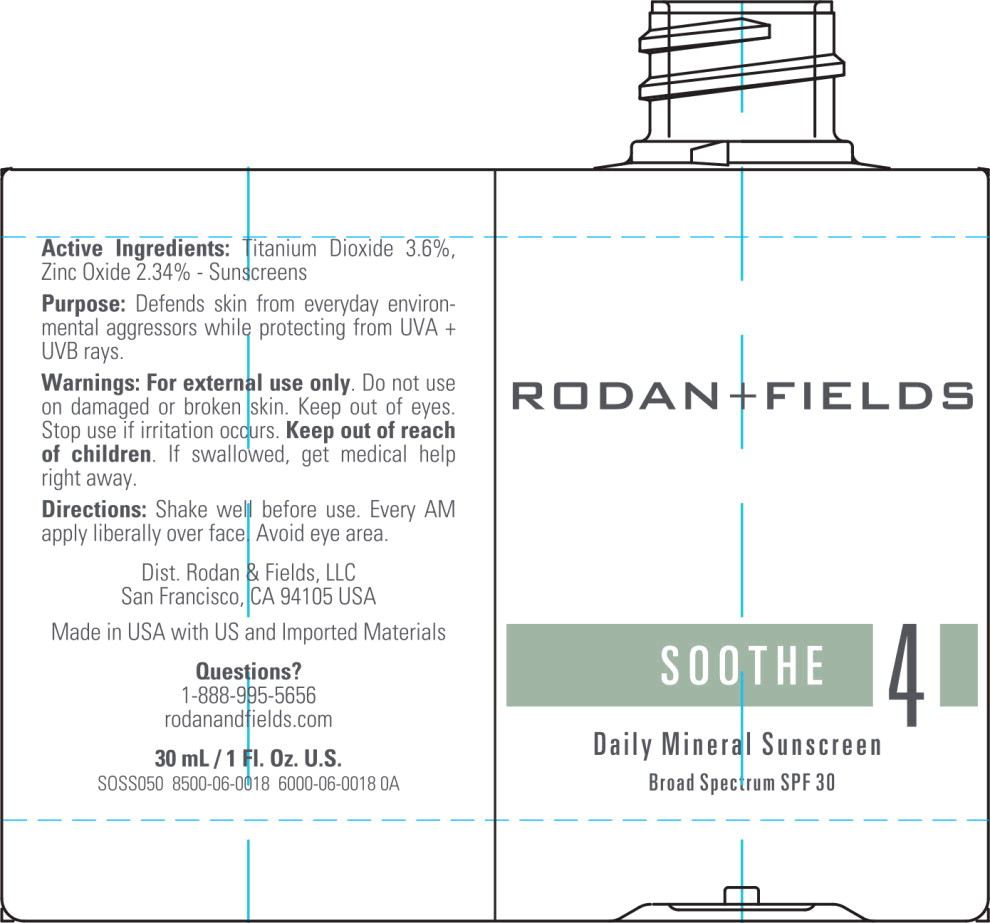 DRUG LABEL: SOOTHE Daily Mineral Sunscreen
NDC: 14222-2440 | Form: LOTION
Manufacturer: Rodan & Fields
Category: otc | Type: HUMAN OTC DRUG LABEL
Date: 20231130

ACTIVE INGREDIENTS: TITANIUM DIOXIDE 0.036 g/1 mL; ZINC OXIDE 0.0234 g/1 mL
INACTIVE INGREDIENTS: 3-(TRIETHOXYSILYL)PROPYLAMINE; AMMONIA; BUTYLENE GLYCOL; BUTYLOCTYL SALICYLATE; ALKYL (C12-15) BENZOATE; CALCIUM GLUCONATE; MEDIUM-CHAIN TRIGLYCERIDES; CAPRYLYL TRISILOXANE; CYNARA SCOLYMUS LEAF; DIMETHICONE; DIMETHICONE/PEG-10/15 CROSSPOLYMER; DIPROPYLENE GLYCOL; DISTEARDIMONIUM HECTORITE; ETHYLHEXYLGLYCERIN; GLUCONOLACTONE; GLYCERIN; ISODODECANE; ISOSTEARIC ACID; MAGNESIUM SULFATE, UNSPECIFIED FORM; NYLON-12; PEG-9 POLYDIMETHYLSILOXYETHYL DIMETHICONE; PENTYLENE GLYCOL; PHENETHYL BENZOATE; PHENOXYETHANOL; POLYGLYCERYL-3 PENTARICINOLEATE; POLYHYDROXYSTEARIC ACID (2300 MW); PROPANEDIOL; PROPYLENE CARBONATE; ROSMARINIC ACID; RUTIN; SILICON DIOXIDE; SODIUM BENZOATE; SODIUM CITRATE, UNSPECIFIED FORM; STEARIC ACID; TOCOPHEROL; TRIETHYLHEXANOIN; WATER

Drug Facts

Active Ingredients

Titanium Dioxide 3.6%

Zinc Oxide 2.34%

Purpose

Sunscreen

Uses

- Helps prevent sunburn.
- When used as directed with other sun protection measures (see Directions), decreases the risk of skin cancer and early skin aging caused by the sun.

Warnings

For external use only.

Do not use on

- damaged or broken skin.

When using this product

- keep out of eyes. Rinse with water to remove.

Stop use and ask doctor if

- rash occurs.

Keep out of reach of children.

If swallowed, get medical help or contact a Poison Control Center right away.

Directions

- Shake well before use.
- Every AM, apply liberally and evenly over face + neck 15 minutes before sun exposure.
- Reapply at least every 2 hours.
- Reapply after 40 minutes of swimming or sweating and after towel drying.
- Sun Protection Measures: Spending time in the sun increases your risk of skin cancer and early skin aging. To decrease this risk, regularly use a sunscreen with a broad spectrum SPF value of 15 or higher and other sun protection measures including:
  - Limit time in the sun, especially from 10 AM - 2 PM.
  - Wear long-sleeve shirts, pants, hats and sunglasses.
- Children under 6 months:
  Ask a doctor.

Other Information

Protect this product from excessive heat and direct sun.

Inactive Ingredients

Acrylates/Dimethicone Copolymer, Aminopropyl Triethoxysilane, Ammonium Hydroxide, Aqua/Eau/Water, Butylene Glycol, Butyloctyl Salicylate, C12-15 Alkyl Benzoate, Calcium Gluconate, Caprylic/Capric Triglyceride, Caprylyl Methicone, Cynara Scolymus (Artichoke) Leaf Extract, Dimethicone, Dimethicone/PEG-10/15 Crosspolymer, Dipropylene Glycol, Disteardimonium Hectorite, Ethylhexylglycerin, Gluconolactone, Glycerin, Isododecane, Isostearic Acid, Magnesium Sulfate, Methyl Carboxymethylphenyl Aminocarboxypropylphosphonate, Nylon-12, PEG-9 Polydimethylsiloxyethyl Dimethicone, Pentylene Glycol, Phenethyl Benzoate, Phenoxyethanol, Polyglyceryl-3 Polyricinoleate, Polyhydroxystearic Acid, Propanediol, Propylene Carbonate, Rosmarinic Acid, Rutin, Silica, Sodium Benzoate, Sodium Citrate, Stearic Acid, Styrene/Acrylates Copolymer, Tocopherol, Triethylhexanoin.

Questions?

1-888-995-5656

Principal Display Panel - 30 mL Carton Label

RODAN+FIELDS

SOOTHE

Daily Mineral Sunscreen

Broad Spectrum SPF 30

4

30 mL/ 1 Fl. Oz. U.S.

Principal Display Panel - 30 mL Tube Label

RODAN+FIELDS

SOOTHE

4

Daily Mineral Sunscreen

Broad Spectrum SPF 30